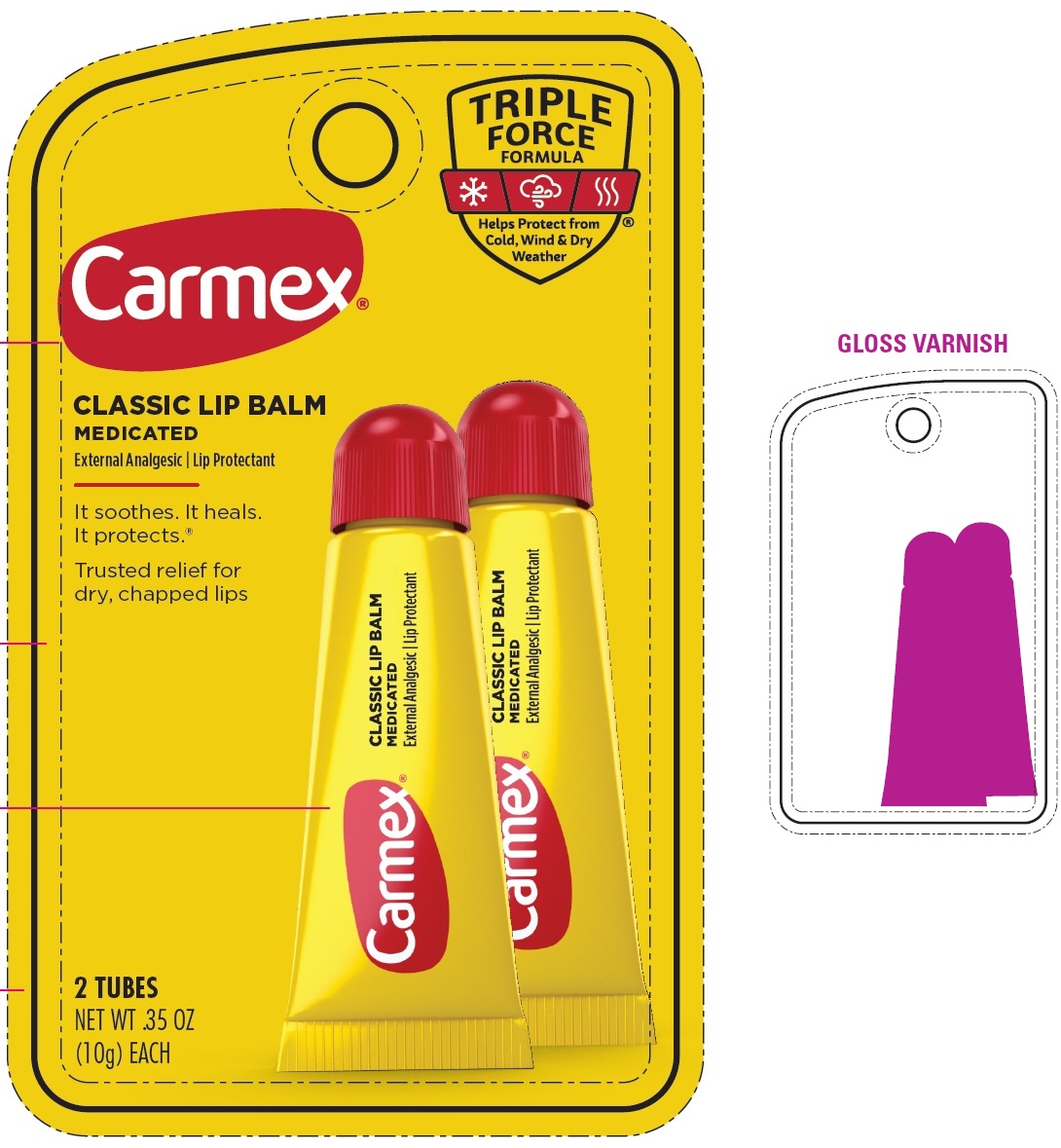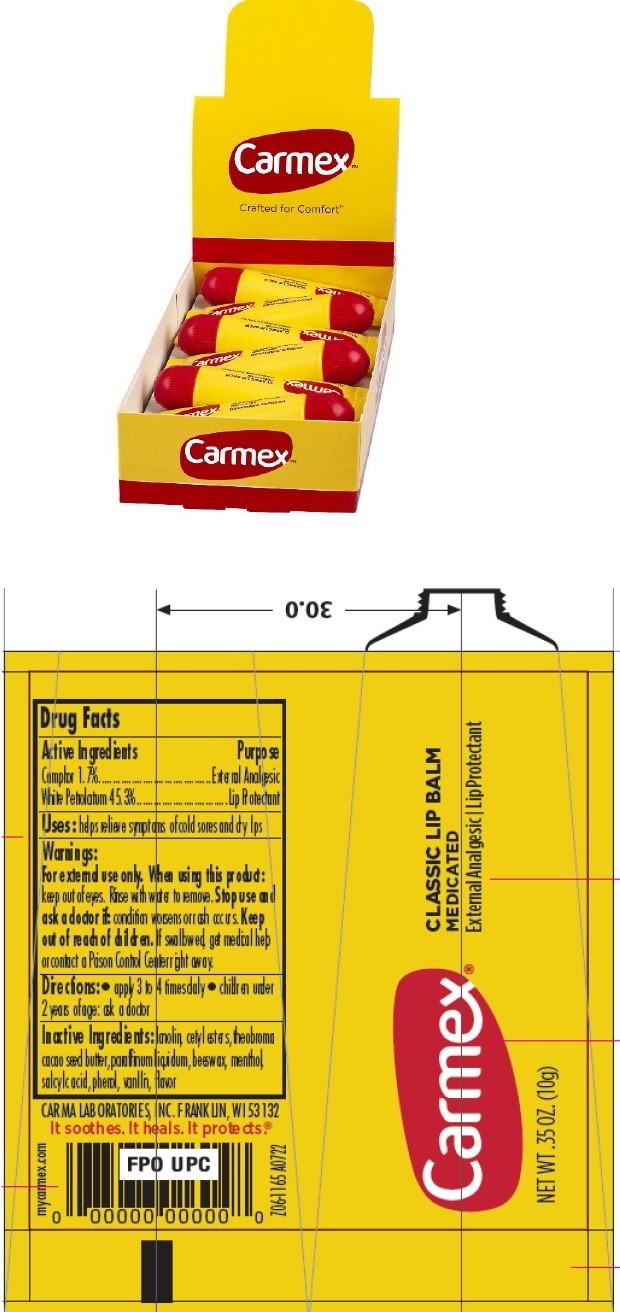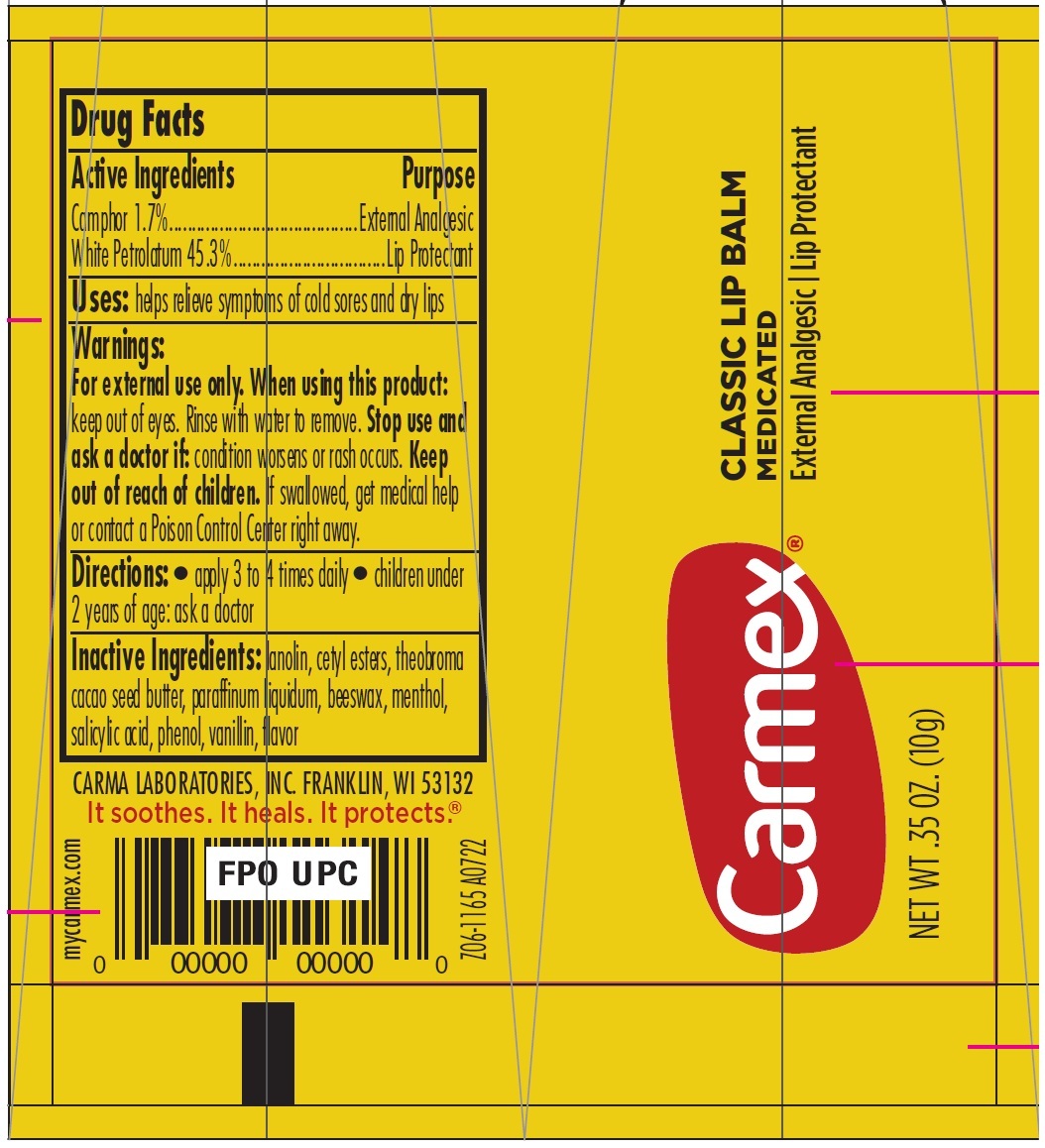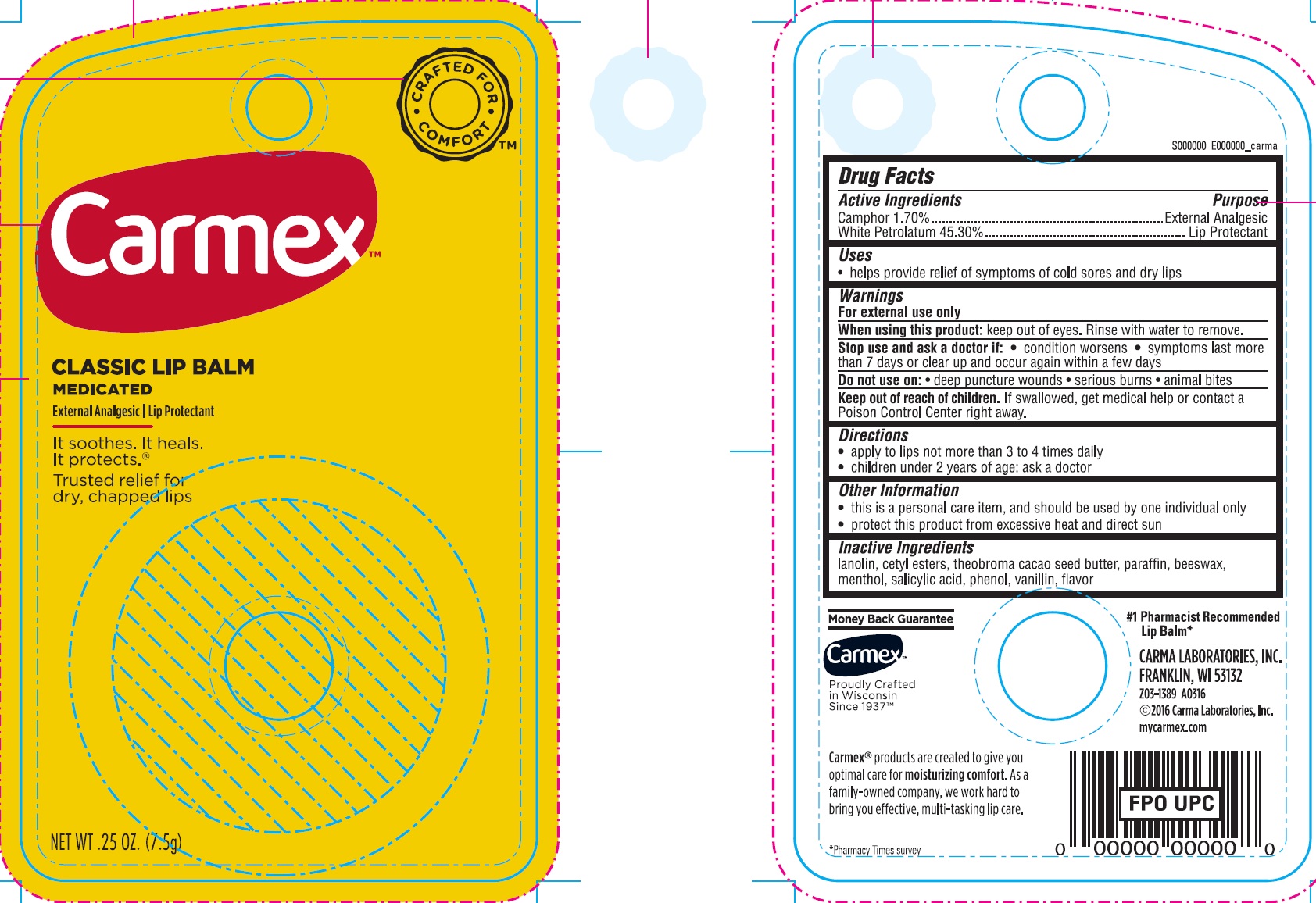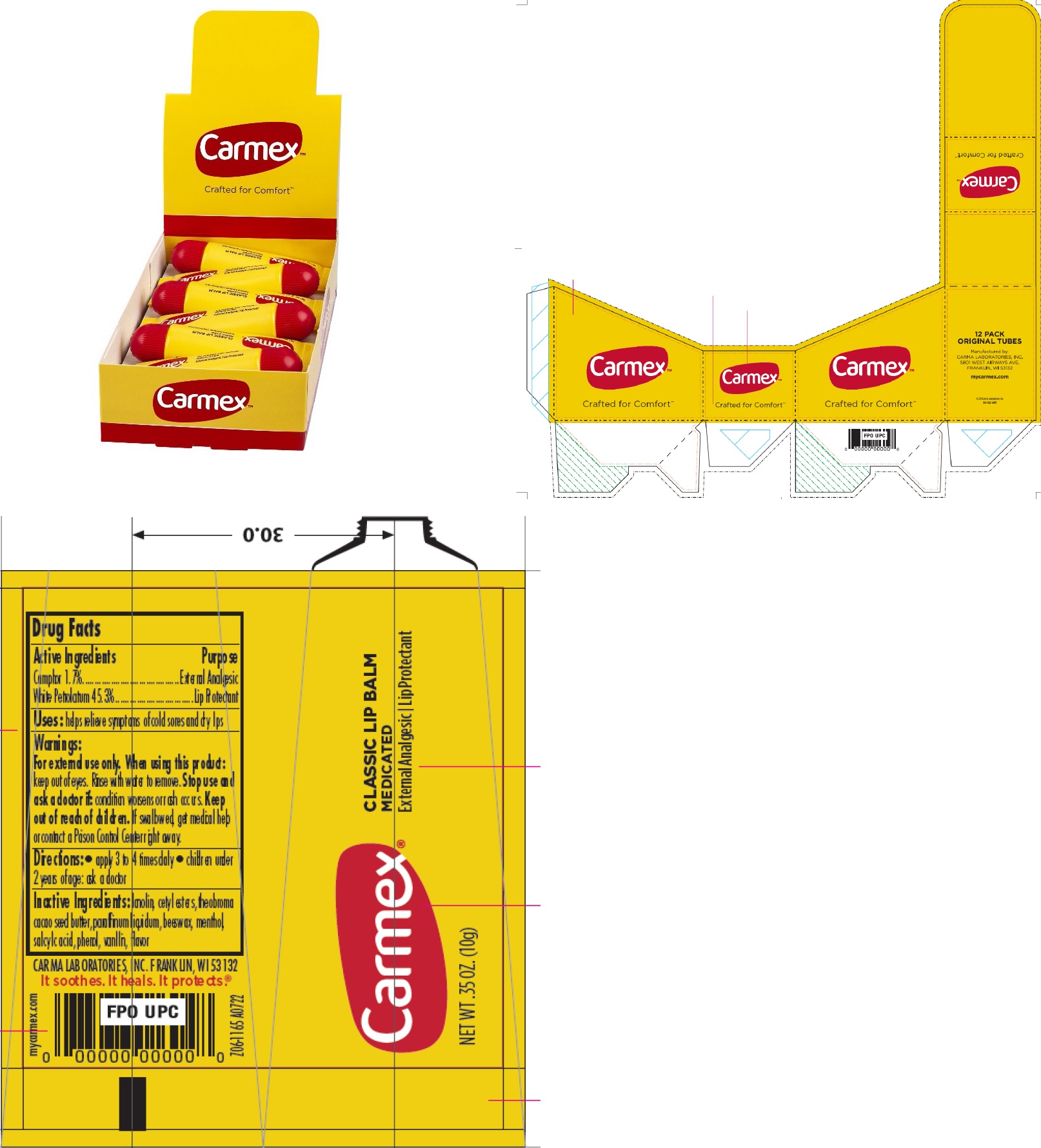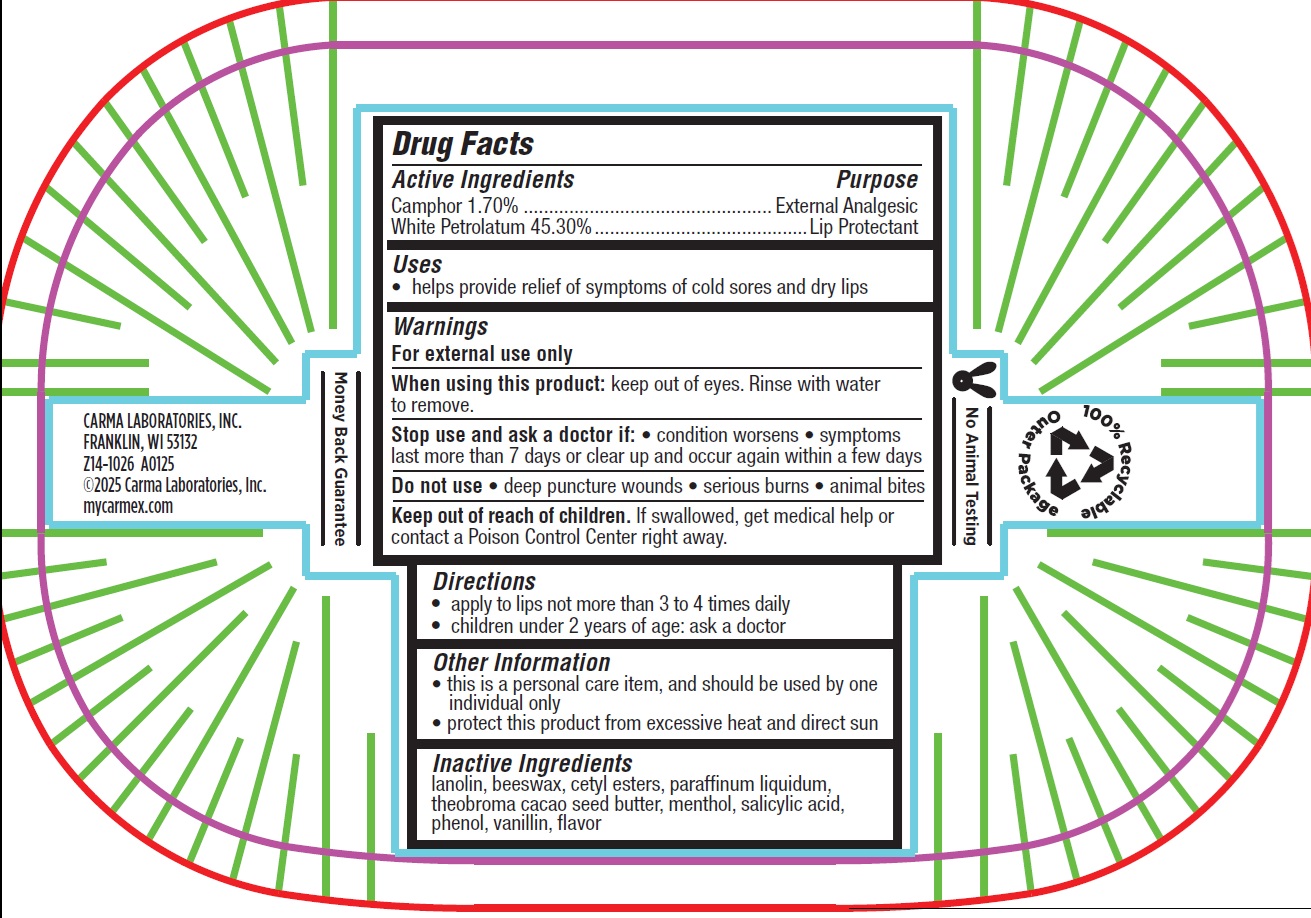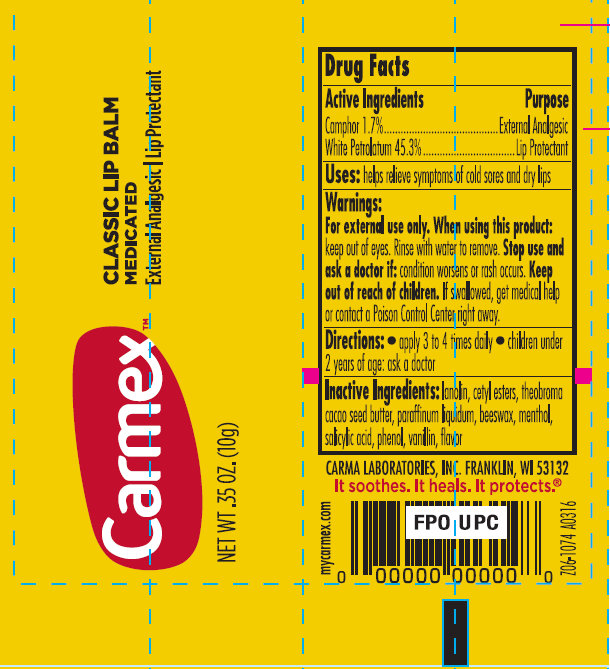 DRUG LABEL: Carmex Classic Lip Balm Medicated
NDC: 10210-0022 | Form: SALVE
Manufacturer: Carma Laboratories, Inc.
Category: otc | Type: HUMAN OTC DRUG LABEL
Date: 20250320

ACTIVE INGREDIENTS: CAMPHOR (SYNTHETIC) 1.7 g/100 g; WHITE PETROLATUM 45.3 g/100 g
INACTIVE INGREDIENTS: LANOLIN; CETYL ESTERS WAX; COCOA BUTTER; PARAFFIN; YELLOW WAX; MENTHOL; SALICYLIC ACID; PHENOL; VANILLA

Carmex Classic Lip Balm Medicated

Active Ingredients

Camphor 1.70%

White Petrolatum 45.30%

Purpose

External Analgesic

Lip Protectant

Uses

- helps provide relief of symptoms of cold sores and dry lips

Warnings

For external use only

When using this product:

keep out of eyes. Rinse with water to remove.

Stop use and ask a doctor if:

- condition worsens • symptoms last more than 7 days or clear up and occur again within a few days

Do not use on:

• deep puncture wounds • serious burns • animal bites

Keep out of reach of children.

If swallowed, get medical help or contact a Poison Control Center right away.

Directions

- apply to lips not more than 3 to 4 times daily
- children under 2 years of age: ask a doctor

Other Information

- this is a personal care item, and should be used by one individual only
- protect this product from excessive heat and direct sun

Inactive Ingredients

lanolin, cetyl esters, theobroma cacao seed butter, paraffin, beeswax, menthol, salicylic acid, phenol, vanillin, flavor